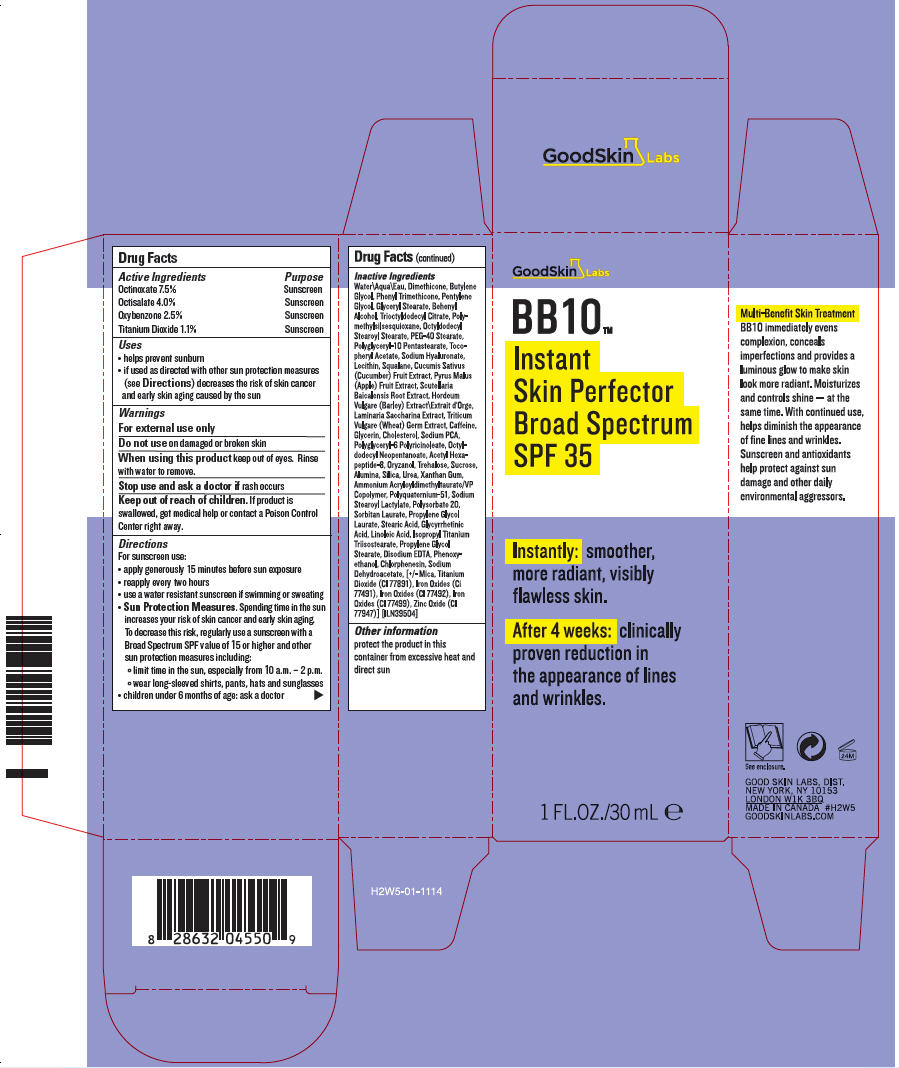 DRUG LABEL: BB10 INSTANT SKIN PERFECTOR BROAD SPECTRUM 
NDC: 68758-010 | Form: LIQUID
Manufacturer: GOOD SKIN DERMACARE
Category: otc | Type: HUMAN OTC DRUG LABEL
Date: 20121004

ACTIVE INGREDIENTS: OCTINOXATE 0.08175 g/1 mL; OCTISALATE 0.0436 g/1 mL; OXYBENZONE 0.02725 g/1 mL; TITANIUM DIOXIDE 0.01199 g/1 mL
INACTIVE INGREDIENTS: Water; Dimethicone; Butylene Glycol; Phenyl Trimethicone; Pentylene Glycol; Glyceryl Monostearate; Docosanol; Trioctyldodecyl Citrate; Octyldodecyl Stearoyl Stearate; PEG-40 Stearate; .Alpha.-Tocopherol Acetate; Hyaluronate Sodium; Squalane; Cucumber; Apple; Scutellaria Baicalensis Root; Barley; Saccharina Latissima; Wheat Germ; Caffeine; Glycerin; Cholesterol; Sodium Pyrrolidone Carboxylate; Octyldodecyl Neopentanoate; Acetyl Hexapeptide-8; Gamma Oryzanol; Trehalose; Sucrose; Aluminum Oxide; Silicon Dioxide; Urea; Xanthan Gum; Ammonium Acryloyldimethyltaurate/VP Copolymer; Sodium Stearoyl Lactylate; Polysorbate 20; Sorbitan Monolaurate; Propylene Glycol Monolaurate; Stearic Acid; Enoxolone; Linoleic Acid; Isopropyl Titanium Triisostearate; Propylene Glycol Stearate; Edetate Disodium; Phenoxyethanol; Chlorphenesin; Sodium Dehydroacetate; Mica; Ferric Oxide Red; Ferric Oxide Yellow; Ferrosoferric Oxide; Zinc Oxide

BB10™ INSTANT SKIN PERFECTOR BROAD SPECTRUM SPF 35

Drug Facts

ACTIVE INGREDIENT

Active Ingredients | Purpose
Octinoxate 7.5% | Sunscreen
Octisalate 4.0% | Sunscreen
Oxybenzone 2.5% | Sunscreen
Titanium Dioxide 1.1% | Sunscreen

Uses

- helps prevent sunburn
- if used as directed with other sun protection measures (see Directions) decreases the risk of skin cancer and early skin aging caused by the sun

Warnings

For external use only

Do not use on damaged or broken skin

When using this product keep out of eyes. Rinse with water to remove.

Stop use and ask a doctor if rash occurs

Keep out of reach of children. If product is swallowed, get medical help or contact a Poison Control Center right away.

Directions

For sunscreen use:

- apply generously 15 minutes before sun exposure
- reapply every two hours
- use a water resistant sunscreen if swimming or sweating
- Sun Protection Measures. Spending time in the sun increases your risk of skin cancer and early skin aging. To decrease this risk, regularly use a sunscreen with a Broad Spectrum SPF value of 15 or higher and other sun protection measures including:
  - limit time in the sun, especially from 10 a.m. – 2 p.m.
  - wear long-sleeved shirts, pants, hats and sunglasses
- children under 6 months of age: ask a doctor

Inactive Ingredients

Water\Aqua\Eau, Dimethicone, Butylene Glycol, Phenyl Trimethicone, Pentylene Glycol, Glyceryl Stearate, Behenyl Alcohol, Trioctyldodecyl Citrate, Polymethylsilsesquioxane, Octyldodecyl Stearoyl Stearate, PEG-40 Stearate, Polyglyceryl-10 Pentastearate, Tocopheryl Acetate, Sodium Hyaluronate, Lecithin, Squalane, Cucumis Sativus (Cucumber) Fruit Extract, Pyrus Malus (Apple) Fruit Extract, Scutellaria Baicalensis Root Extract, Hordeum Vulgare (Barley) Extract\Extrait d'Orge, Laminaria Saccharina Extract, Triticum Vulgare (Wheat) Germ Extract, Caffeine, Glycerin, Cholesterol, Sodium PCA, Polyglyceryl-6 Polyricinoleate, Octyldodecyl Neopentanoate, Acetyl Hexapeptide-8, Oryzanol, Trehalose, Sucrose, Alumina, Silica, Urea, Xanthan Gum, Ammonium Acryloyldimethyltaurate/VP Copolymer, Polyquaternium-51, Sodium Stearoyl Lactylate, Polysorbate 20, Sorbitan Laurate, Propylene Glycol Laurate, Stearic Acid, Glycyrrhetinic Acid, Linoleic Acid, Isopropyl Titanium Triisostearate, Propylene Glycol Stearate, Disodium EDTA, Phenoxyethanol, Chlorphenesin, Sodium Dehydroacetate, [+/- Mica, Titanium Dioxide (CI 77891), Iron Oxides (Ci 77491), Iron Oxides (CI 77492), Iron Oxides (CI 77499), Zinc Oxide (CI 77947)] [ILN39504]

Other information

protect the product in this container from excessive heat and direct sun

GOOD SKIN LABS, DIST.
NEW YORK, NY 10153

PRINCIPAL DISPLAY PANEL - 30 mL Bottle Carton

GoodSkin Labs

BB10™
Instant
Skin Perfector
Broad Spectrum
SPF 35

Instantly: smoother,
more radiant, visibly
flawless skin.

After 4 weeks: clinically
proven reduction in
the appearance of lines
and wrinkles.

1 FL.OZ./30 mL e